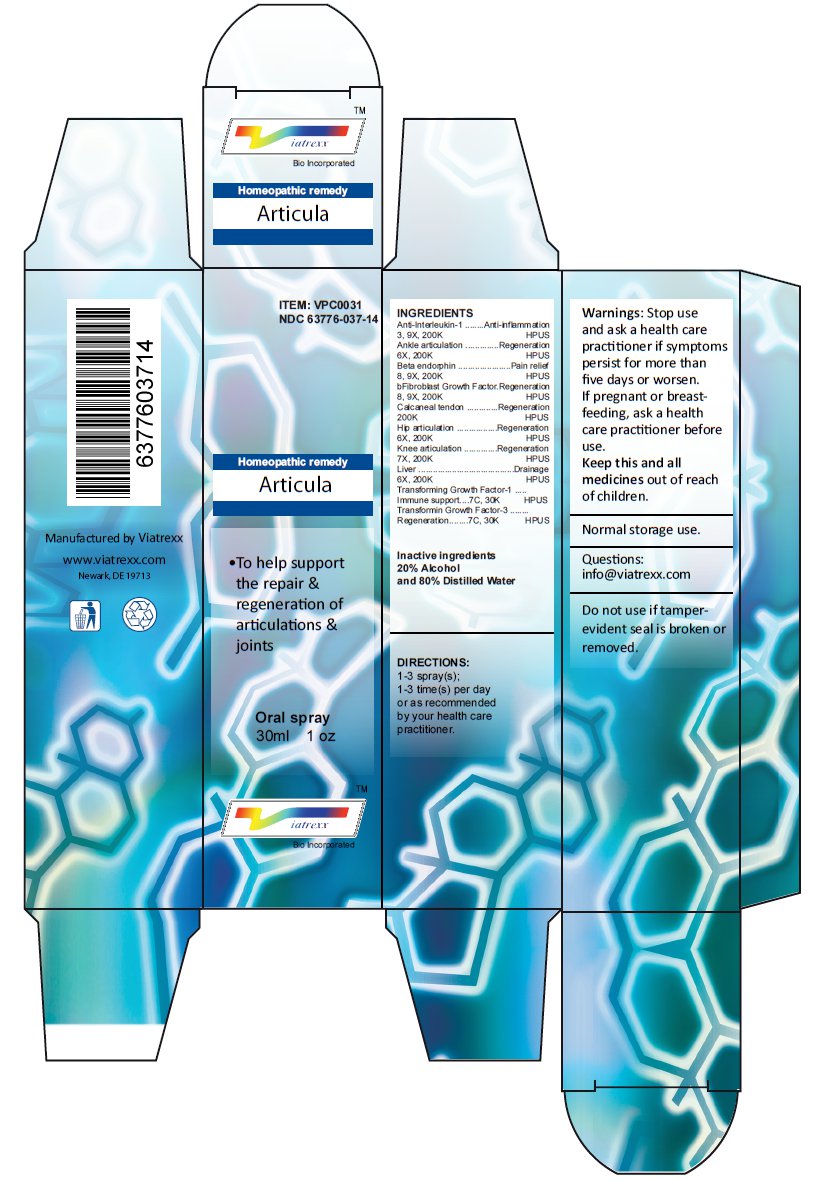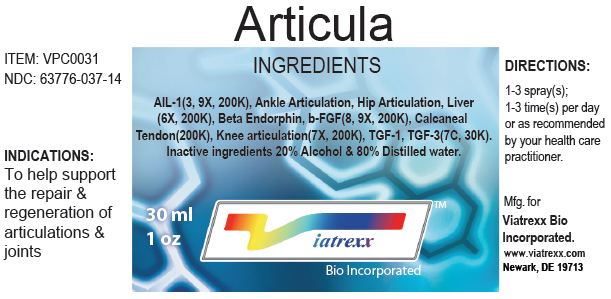 DRUG LABEL: Articula
NDC: 63776-037 | Form: SPRAY
Manufacturer: VIATREXX BIO INCORPORATED
Category: homeopathic | Type: HUMAN OTC DRUG LABEL
Date: 20221130

ACTIVE INGREDIENTS: ANTI-INTERLEUKIN-1.ALPHA. IMMUNOGLOBULIN G RABBIT 200 [kp_C]/1 mL; BOS TAURUS ANKLE JOINT 200 [kp_C]/1 mL; SUS SCROFA ANKLE JOINT 200 [kp_C]/1 mL; METENKEFALIN 200 [kp_C]/1 mL; ERSOFERMIN 200 [kp_C]/1 mL; BOS TAURUS ACHILLES TENDON 200 [kp_C]/1 mL; SUS SCROFA ACHILLES TENDON 200 [kp_C]/1 mL; BOS TAURUS HIP JOINT 200 [kp_C]/1 mL; SUS SCROFA HIP JOINT 200 [kp_C]/1 mL; BOS TAURUS KNEE JOINT 200 [kp_C]/1 mL; SUS SCROFA KNEE JOINT 200 [kp_C]/1 mL; BEEF LIVER 200 [kp_C]/1 mL; PORK LIVER 200 [kp_C]/1 mL; TRANSFORMING GROWTH FACTOR BETA-1 30 [kp_C]/1 mL; AVOTERMIN 30 [kp_C]/1 mL
INACTIVE INGREDIENTS: ALCOHOL; WATER

Articula

Active Ingredients

Anti-Interleukin-1 3 9X 200K, Ankle articulation 6X 200K, Beta endorphin 8 9X 200K, bFibroblast Growth Factor 8 9X 200K, Calcaneal tendon 200K, Hip articulation 6X 200K, Knee articulation 7X 200K, Liver 6X 200K, Transforming Growth Factor-1 7C 30K, Transformin Growth Factor-3 7C 30K,

Purpose

Anti-Interleukin-1 | Anti-inflammation
Ankle articulation | Regeneration
Beta endorphin | Pain relief
bFibroblast Growth Factor | Regeneration
Calcaneal tendon | Regeneration
Hip articulation | Regeneration
Knee articulation | Regeneration
Liver | Drainage
Transforming Growth Factor-1 | Immune support
Transformin Growth Factor-3 | Regeneration

Uses

To help support the repair & regeneration of articulations & joints

Warnings

Stop use and ask a health care practitioner if symptoms persist for more than five days or worsen. If pregnant or breastfeeding, ask a health care practitioner before use.

KEEP OUT OF REACH OF CHILDREN

Keep this and all medicines out of reach of children.

Directions

1-3 spray(s); 1-3 time(s) per day or as recommended by your health care practitioner.

Other Ingredients

Alcohol and Water

Other Information

Normal storage use.
Do not use if tamper-evident seal is broken or removed.

Principal Display Panel

ITEM: VPC0031
NDC 63776-037-14
Homeopathic remedy
Articula
• To help support the repair & regeneration of articulations & joints
Oral spray
30ml 1 oz
Viatrexx™ Bio Incorporated
Manufactured by Viatrexx
www.viatrexx.com
Newark, DE 19713

Articula
30 mL
1 oz
Viatrexx™ Bio Incorporated
ITEM: VPC0031
NDC: 63776-037-14
INDICATIONS:
To help support the repair & regeneratin of articulations & joints
DIRECTIONS:
1-3 spray(s); 1-3 time(s) per day or as recommended by your health care practitioner.
Mfg. for
Viatrexx Bio Incorporated.
www.viatrexx.com
Newark, DE 19713